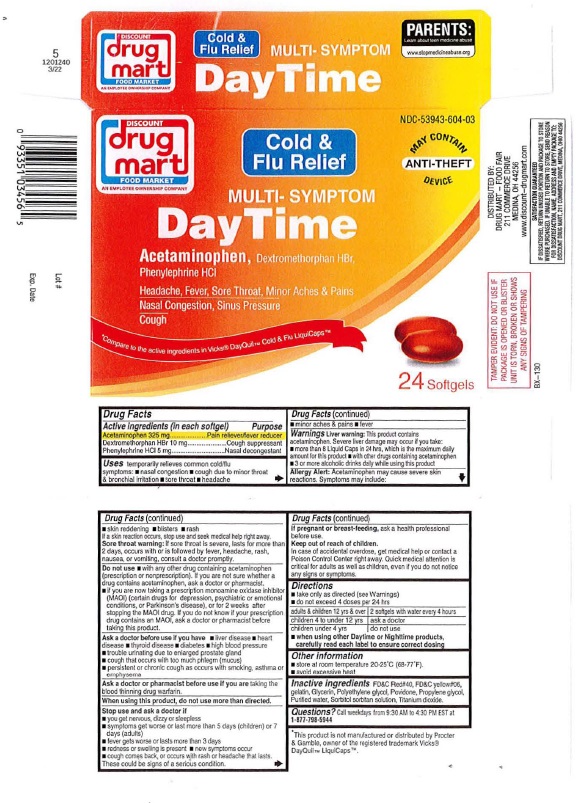 DRUG LABEL: Day Time Multi-Symptom Cold and Flu Relief
NDC: 53943-604 | Form: CAPSULE, LIQUID FILLED
Manufacturer: Discount Drug Mart
Category: otc | Type: HUMAN OTC DRUG LABEL
Date: 20231117

ACTIVE INGREDIENTS: ACETAMINOPHEN 325 mg/1 1; DEXTROMETHORPHAN HYDROBROMIDE 10 mg/1 1; PHENYLEPHRINE HYDROCHLORIDE 5 mg/1 1
INACTIVE INGREDIENTS: FD&C RED NO. 40; FD&C YELLOW NO. 6; GELATIN; GLYCERIN; POLYETHYLENE GLYCOL, UNSPECIFIED; POVIDONE; PROPYLENE GLYCOL; WATER; SORBITOL SOLUTION; TITANIUM DIOXIDE

DISCOUNT drug mart Day Time Multi-Symptom Cold & Flu Relief

Drug Facts

Active ingredients (in each Softgel)

Acetaminophen 325 mg
Dextromethorphan HBr 10 mg
Phenylephrine HCI 5 mg

Purpose
Acetaminophen Pain reliever/Fever reducer
Dextromethorphan HBr Cough suppressant
Phenylephrine HCI Nasal Decongestant

Uses
temporarily relieves common cold and flu symptoms:
• nasal congestion
• cough due to minor throat and bronchial irritation
• sore throat
• headache
• minor aches and pain
• fever

Warnings
Liver warning: This product contains
acetaminophen. Severe liver damage may occur if you take:
• more than 8 Liquid Caps in 24 hours • which is the maximum daily
amount for this product • with other drugs containing acetaminophen
• 3 or more alcoholic drinks daily while using this product
Allergy alert: Acetaminophen may cause severe skin
reactions. Symptoms may include
• skin reddening • blisters • rash.
If a skin reaction occurs, stop use and seek medical help right away.
Sore throat warning: If sore throat is severe, lasts for more than
2 days, occurs with or is followed by fever, headache, rash,
nausea or vomiting, consult a doctor promptly.

Do not use: • with any other drug containing acetaminophen
(prescription or nonprescription). If you are not sure whether a
drug contains acetaminophen, ask a doctor or pharmacist
• if you are now taking a prescription monoamine oxidase inhibitor
(MAOI) (certain drugs for depression, psychiatric, or emotional
conditions, or Parkinson's disease), or for 2 weeks after
stopping the MAOI drug. If you do not know if your prescription
drug contains an MAOI, ask a doctor or pharmacist before
taking this product.

Ask a doctor before use if you have • liver disease • heart
disease • thyroid disease • diabetes • high blood pressure
• trouble urinating due to an enlarged prostate gland
• cough that occurs with too much phlegm (mucus)
• persistent or chronic cough such as occurs with smoking, asthma or
emphysema

Ask a doctor or pharmacist before use if you are taking the

blood thinning drug warfarin.

When using this product, do not use more than directed.

Stop use and ask a doctor if
• you get nervous, dizzy or sleepless
• symptoms get worse or last 1) more than 5 days (children) or 7
days (adults)
• fever gets worse or lasts more than 3 days • redness
or swelling is present • new symptoms occur
• cough comes back, or occurs with rash or headache that lasts.
These could be signs of a serious condition.

PREGNANCY OR BREAST FEEDING

If pregnant or breast feeding, ask a health professional before use.

Keep out of reach of children.
In case of accidental overdose, get medical help or contact a
Poison Control Center right away. Quick medical attention is
critical for adults as well as for children, even if you do not notice
any signs or symptoms.

Directions
• take only as directed (see Warning)
• do not exceed 4 doses per 24 hours

adults and Children 12 yrs & over | 2 softgels with water every 4 hours
children 4 to under 12 yrs | ask a doctor
children under 4 years | do not use

• when using olher Daytime or Nighttime producls,
carefully read each label to ensure correcl dosing

Other information

• store at room temperature 20-2S·C (68-77"F)
• avoid excessive heat

INACTIVE INGREDIENT

Inactive ingredientsFD&C Red #40, FD&C Yellow #06,

gelatin, Glycerin, Polyethylene glycol, Povidone, Propylene glycol,

Purified water, Sorbitol sorbitan solution, Titanium dioxide.

QUESTIONS

Questions? Call Weekdays from 9:30 AM to 4:30 PM EST at 1-877-798-5944

Package Labeling: DISCOUNT drug mart Day Time Multi-Symptom Cold & Flu Relief

DISCOUNT NDC-53943-604-03

drug mart

FOOD MARKET

Cold &
Flu Relief

MULTI-SYMPTOM

DAY TIME

*Compare to the active ingredients in Vicks® DayQuil™ Cold & Flu LiquiCaps™

24 Softgels

DISTRIBUTED BY:

DRUG MART - FOOD FAIR

211 COMMERCE DRIVE

MEDINA, OH 44256

www.discount-drugmart.com

This product is not manufactured or distributed by Procter
& Gamble, owner of the registered trademark Vicks®
DayOuilTM LiquiCapsTM

TAMPER EVIDENT: DO NOT USE IF

PACKAGE IS OPENED OR BLISTER

UNIT IS TORN, BROKEN OR SHOWS

ANY SIGNS OF TAMPERING

IF DISSATISFIED, RETURN UNUSED PORTION AND PACKAGE TO STORE

WHERE PURCHASED. IF UNABLE TO RETURN TO STORE, SEND REASON

FOR DISSATISFACTION , NAME, ADDRESS AND EMPTY PACKAGE TO:

DISCOUNT DRUG MART, 211 COMMERCE DRIVE MEDINA, OHIO 44256